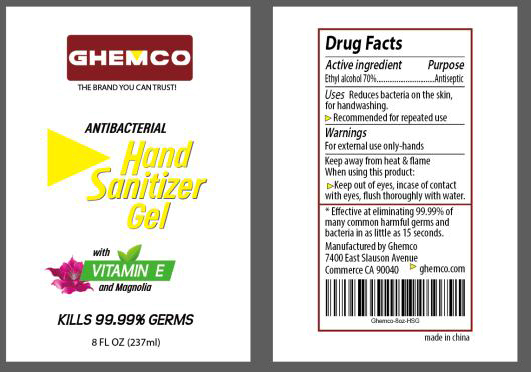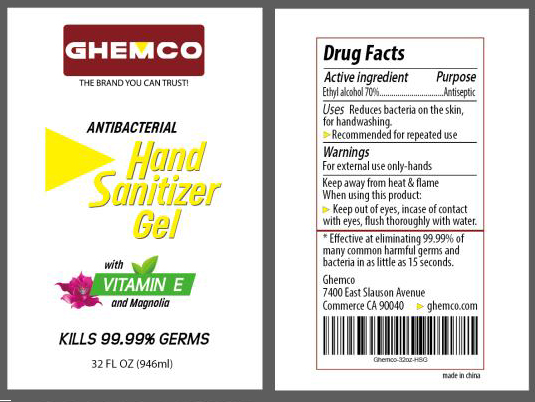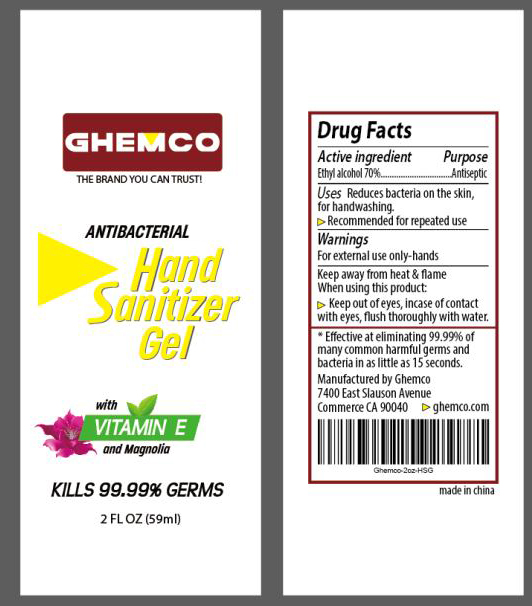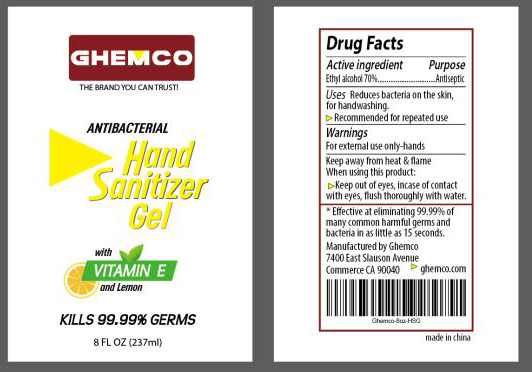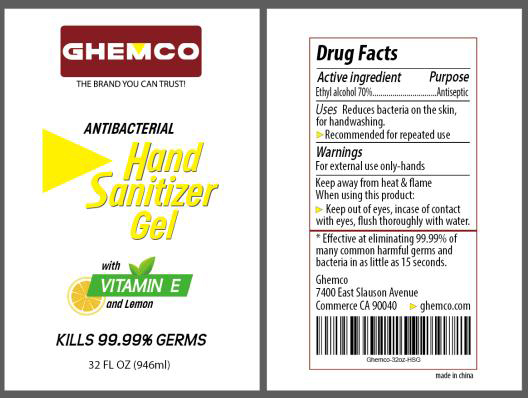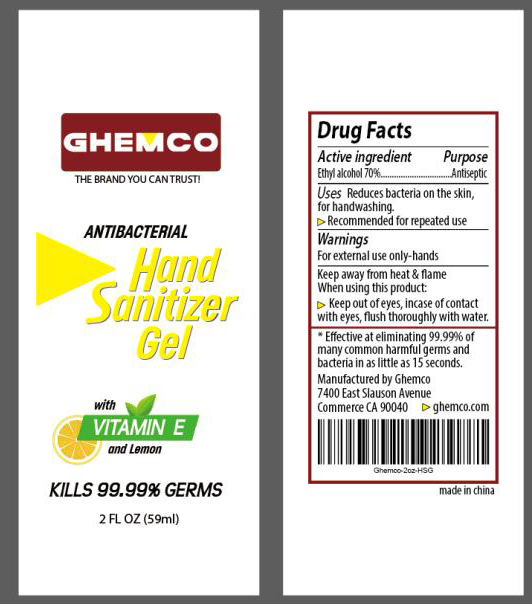 DRUG LABEL: Hand Sanitizer
NDC: 80796-001 | Form: GEL
Manufacturer: Ghemco Llc
Category: otc | Type: HUMAN OTC DRUG LABEL
Date: 20201015

ACTIVE INGREDIENTS: ALCOHOL 70 mL/100 mL
INACTIVE INGREDIENTS: GLYCERIN; WATER

Hand sanitizer

Active ingredient

Ethyl alcohol 70% Antiseptic

Purpose

Antiseptic, Hand Sanitizer

Uses

Reduces bacteria on the skin, for handwashing.

Recommended for repeated use

Warnings

For external use only-hands

Keep away from heat & flame

When using this product

Keep of eyes. In case of contact with eyes, flush thoroughly with water.

Keep out of reach of children

INACTIVE INGREDIENT

water, glycerol

DOSAGE AND ADMINISTRATION

Effective at eliminating 99.99% of many common harmful gems and bacteria in as little as 15 seconds

Package Label - Principal Display Panel

237 mL NDC: 80796-001-02

GHEMCO

THE BRAND YOU CAN TRUST!

ANTIBACTERIAL

HAND SANITIZER GEL

with

VITAMIN E

and Magnolia

KILLS 99.99% GERMS

8 FL OZ (237ml)

946 mL NDC: 80796-001-03

GHEMCO

THE BRAND YOU CAN TRUST!

ANTIBACTERIAL

HAND SANITIZER GEL

with

VITAMIN E

and Magnolia

KILLS 99.99% GERMS

32 FL OZ (946ml)

59 mL NDC: 80796-001-04

GHEMCO

THE BRAND YOU CAN TRUST!

ANTIBACTERIAL

HAND SANITIZER GEL

with

VITAMIN E

and Magnolia

KILLS 99.99% GERMS

2 FL OZ (59ml)

237 mL NDC: 80796-002-02

GHEMCO

THE BRAND YOU CAN TRUST!

ANTIBACTERIAL

HAND SANITIZER GEL

with

VITAMIN E

and Lemon

KILLS 99.99% GERMS

8 FL OZ (237ml)

946 mL NDC: 80796-002-03

GHEMCO

THE BRAND YOU CAN TRUST!

ANTIBACTERIAL

HAND SANITIZER GEL

with

VITAMIN E

and Lemon

KILLS 99.99% GERMS

32 FL OZ (946ml)

59 mL NDC: 80796-002-04

GHEMCO

THE BRAND YOU CAN TRUST!

ANTIBACTERIAL

HAND SANITIZER GEL

with

VITAMIN E

and Lemon

KILLS 99.99% GERMS

2 FL OZ (59ml)